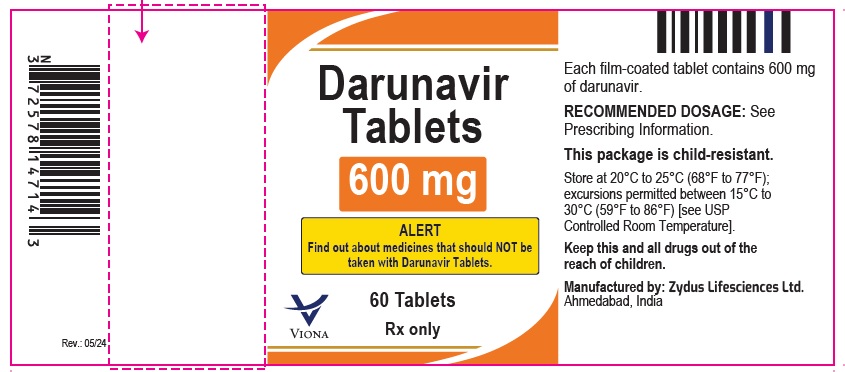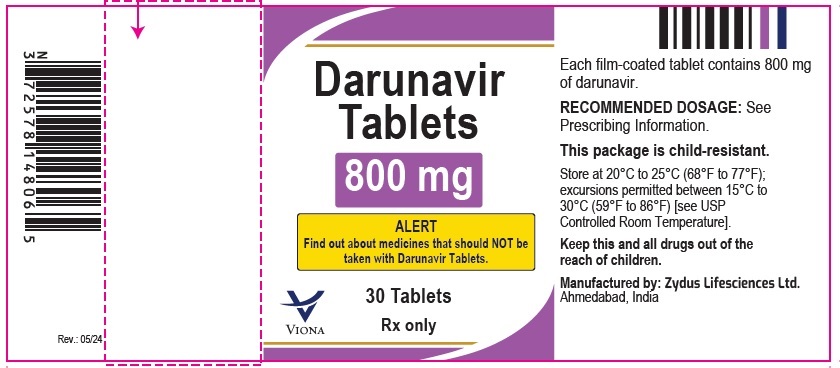 DRUG LABEL: Darunavir
NDC: 70771-1745 | Form: TABLET, FILM COATED
Manufacturer: Zydus Lifesciences Limited
Category: prescription | Type: HUMAN PRESCRIPTION DRUG LABEL
Date: 20240429

ACTIVE INGREDIENTS: DARUNAVIR 600 mg/1 1
INACTIVE INGREDIENTS: FERRIC OXIDE RED; FERRIC OXIDE YELLOW; FERROSOFERRIC OXIDE; HYDROXYPROPYL CELLULOSE, UNSPECIFIED; HYPROMELLOSE 2910 (6 MPA.S); MAGNESIUM STEARATE; MICROCRYSTALLINE CELLULOSE; SILICON DIOXIDE; SODIUM STARCH GLYCOLATE TYPE A POTATO; TALC; TITANIUM DIOXIDE

Darunavir Tablets

PACKAGE LABEL.PRINCIPAL DISPLAY PANEL

NDC 70771-1745-6

Darunavir tablets, 600 mg

60 Tablets

Rx only

NDC 70771-1746-3

Darunavir tablets, 800 mg

30 Tablets

Rx only